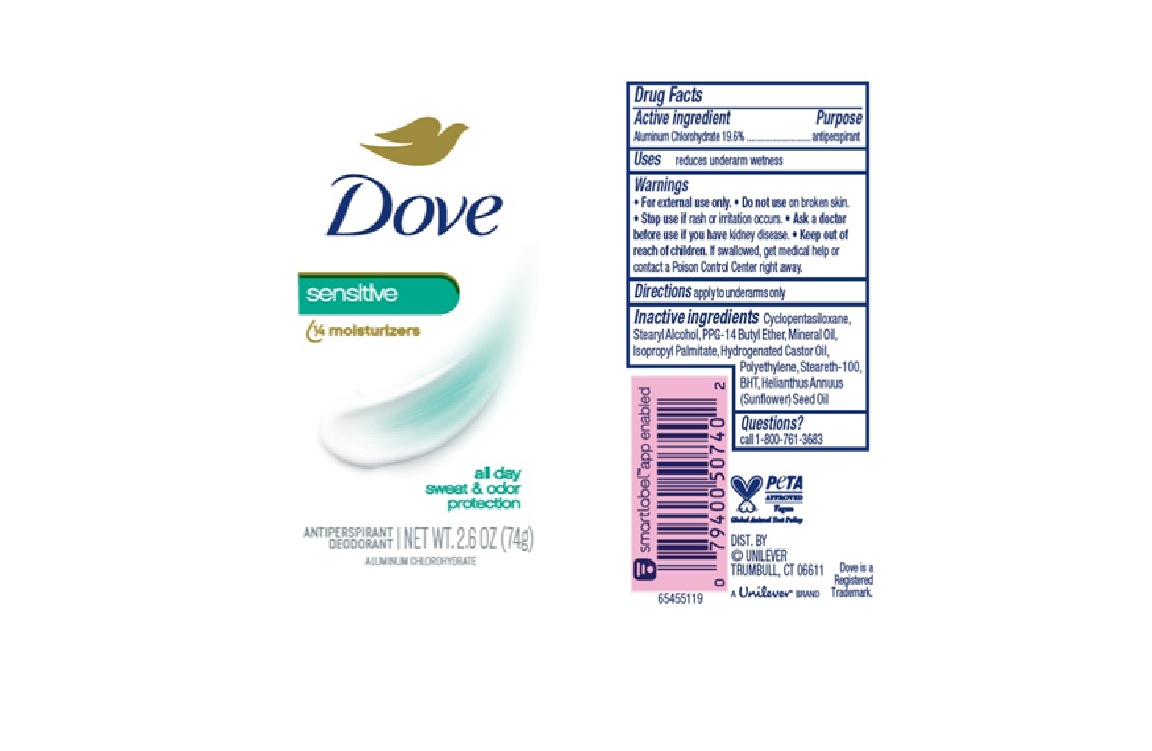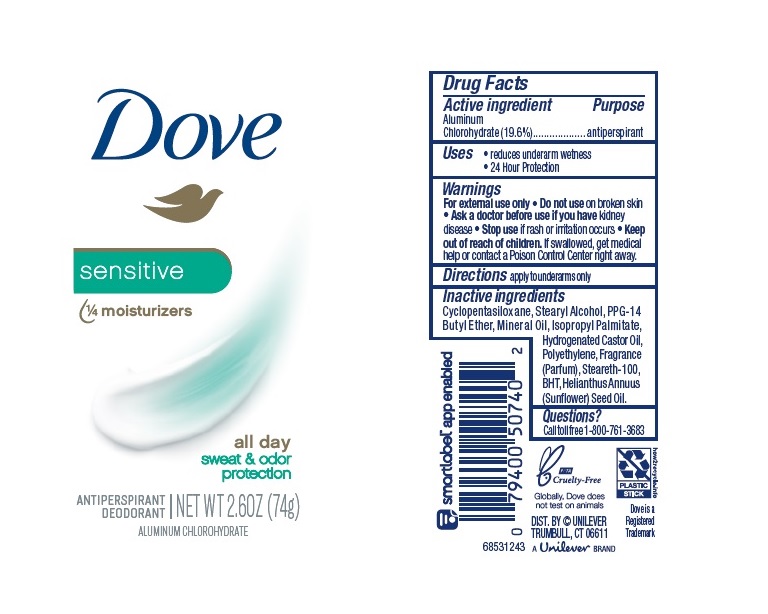 DRUG LABEL: Dove
NDC: 64942-1856 | Form: STICK
Manufacturer: Conopco Inc. d/b/a/ Unilever
Category: otc | Type: HUMAN OTC DRUG LABEL
Date: 20260106

ACTIVE INGREDIENTS: ALUMINUM CHLOROHYDRATE 19.6 g/100 g
INACTIVE INGREDIENTS: HIGH DENSITY POLYETHYLENE; CYCLOMETHICONE 5; HYDROGENATED CASTOR OIL; BUTYLATED HYDROXYTOLUENE; PPG-14 BUTYL ETHER; STEARYL ALCOHOL; SUNFLOWER OIL; MINERAL OIL; STEARETH-100; ISOPROPYL PALMITATE

Dove Sensitive Antiperspirant Deodorant

DOVE SENSITIVE ANTIPERSPIRANT DEODORANT - aluminum chlorohydrate stick

Dove Advanced Care Caring Coconut 48h Antiperspirant Deodorant

Drug Facts

Active ingredient

Aluminum Chlorohydrate (19.6)

Purpose

antiperspirant

Uses

• reduces underarm wetness

• 24 Hour Protection

Warnings

• For external use only.
• Do not use on broken skin .
• Ask a doctor before use if you have kidney disease.
• Stop use if rash or irritation occurs.

• Keep out of reach of children.

If swallowed, get medical help or contact a Poison Control Center right away.

Directions

apply to underarms only

Inactive ingredients

Cyclopentasiloxane, Stearyl Alcohol, PPG-14 Butyl Ether, Mineral Oil, Isopropyl Palmitate, Hydrogenated Castor Oil, Polyethylene, Fragrance (Parfum), Steareth-100, BHT, Helianthus Annuus (Sunflower) Seed Oil.

Questions?

Call toll-free 1-800-761-3683